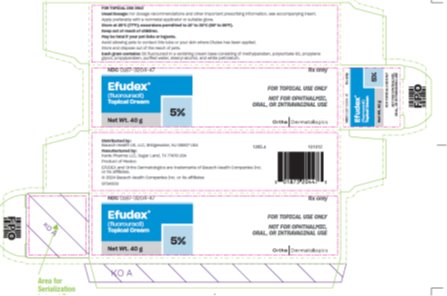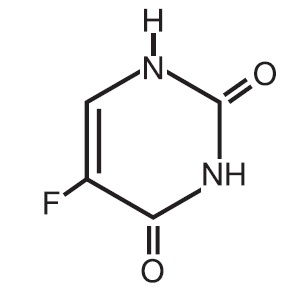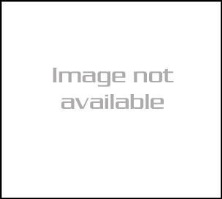 DRUG LABEL: Efudex
NDC: 0187-3202 | Form: SOLUTION
Manufacturer: Bausch Health US, LLC
Category: prescription | Type: HUMAN PRESCRIPTION DRUG LABEL
Date: 20250423

ACTIVE INGREDIENTS: FLUOROURACIL 0.5 g/10 mL
INACTIVE INGREDIENTS: PROPYLENE GLYCOL; TROMETHAMINE; METHYLPARABEN; PROPYLPARABEN; EDETATE DISODIUM; HYDROXYPROPYL CELLULOSE (110000 WAMW)

EFUDEX®
(fluorouracil)
TOPICAL SOLUTIONS AND CREAM
FOR TOPICAL USE ONLY
NOT FOR OPHTHALMIC, ORAL, OR INTRAVAGINAL USE

DESCRIPTION:

EFUDEX Topical Solutions and Cream are topical preparations containing the fluorinated pyrimidine 5-fluorouracil, an antineoplastic antimetabolite.

EFUDEX Topical Solution consists of 2% or 5% fluorouracil on a weight/weight basis, compounded with disodium edetate, hydroxypropyl cellulose, methylparaben, propylene glycol, propylparaben, and tris (hydroxymethyl) aminomethane.

EFUDEX Cream contains 5% fluorouracil in a vanishing cream base consisting of methylparaben, polysorbate 60, propylene glycol, propylparaben, purified water, stearyl alcohol, and white petrolatum.

Chemically, fluorouracil is a 5-fluoro-2,4(1 H,3 H)-pyrimidinedione. It is a white to practically white crystalline powder which is sparingly soluble in water and slightly soluble in alcohol. One gram of fluorouracil is soluble in 100 mL of propylene glycol. The molecular weight of 5-fluorouracil is 130.08 and the structural formula is:

CLINICAL PHARMACOLOGY:

There is evidence that the metabolism of fluorouracil in the anabolic pathway blocks the methylation reaction of deoxyuridylic acid to thymidylic acid. In this manner, fluorouracil interferes with the synthesis of deoxyribonucleic acid (DNA) and to a lesser extent inhibits the formation of ribonucleic acid (RNA). Since DNA and RNA are essential for cell division and growth, the effect of fluorouracil may be to create a thymine deficiency which provokes unbalanced growth and death of the cell. The effects of DNA and RNA deprivation are most marked on those cells which grow more rapidly and take up fluorouracil at a more rapid rate. The catabolic metabolism of fluorouracil results in degradation products (e.g., CO2, urea, α-fluoro-β-alanine) which are inactive.

Systemic absorption studies of topically applied fluorouracil have been performed on patients with actinic keratoses using tracer amounts of^14C-labeled fluorouracil added to a 5% preparation. All patients had been receiving nonlabeled fluorouracil until the peak of the inflammatory reaction occurred (2 to 3 weeks), ensuring that the time of maximum absorption was used for measurement. One gram of labeled preparation was applied to the entire face and neck and left in place for 12 hours. Urine samples were collected. At the end of 3 days, the total recovery ranged between 0.48% and 0.94% with an average of 0.76%, indicating that approximately 5.98% of the topical dose was absorbed systemically. If applied twice daily, this would indicate systemic absorption of topical fluorouracil to be in the range of 5 to 6 mg per daily dose of 100 mg. In an additional study, negligible amounts of labeled material were found in plasma, urine, and expired CO2after 3 days of treatment with topically applied^14C-labeled fluorouracil.

INDICATIONS AND USAGE:

EFUDEX is recommended for the topical treatment of multiple actinic or solar keratoses. In the 5% strength, it is also useful in the treatment of superficial basal cell carcinomas when conventional methods are impractical, such as with multiple lesions or difficult treatment sites. Safety and efficacy in other indications have not been established.

The diagnosis should be established prior to treatment, since this method has not been proven effective in other types of basal cell carcinomas. With isolated, easily accessible basal cell carcinomas, surgery is preferred since success with such lesions is almost 100%. The success rate with EFUDEX Cream and Solution is approximately 93%, based on 113 lesions in 54 patients. Twenty-five lesions treated with the solution produced 1 failure and 88 lesions treated with the cream produced 7 failures.

CONTRAINDICATIONS:

EFUDEX may cause fetal harm when administered to a pregnant woman.

There are no adequate and well-controlled studies in pregnant women with either the topical or the parenteral forms of fluorouracil. One birth defect (cleft lip and palate) has been reported in the newborn of a patient using EFUDEX as recommended. One birth defect (ventricular septal defect) and cases of miscarriage have been reported when EFUDEX was applied to mucous membrane areas. Multiple birth defects have been reported in a fetus of a patient treated with intravenous fluorouracil.

Animal reproduction studies have not been conducted with EFUDEX. Fluorouracil administered parenterally has been shown to be teratogenic in mice, rats, and hamsters when given at doses equivalent to the usual human intravenous dose; however, the amount of fluorouracil absorbed systemically after topical administration to actinic keratoses is minimal (see CLINICAL PHARMACOLOGY). Fluorouracil exhibited maximum teratogenicity when given to mice as single intraperitoneal injections of 10 to 40 mg/kg on Day 10 or 12 of gestation. Similarly, intraperitoneal doses of 12 to 37 mg/kg given to rats between Days 9 and 12 of gestation and intramuscular doses of 3 to 9 mg/kg given to hamsters between Days 8 and 11 of gestation were teratogenic and/or embryotoxic (i.e., resulted in increased resorptions or embryolethality). In monkeys, divided doses of 40 mg/kg given between Days 20 and 24 of gestation were not teratogenic. Doses higher than 40 mg/kg resulted in abortion.

EFUDEX should not be used in patients with dihydropyrimidine dehydrogenase (DPD) enzyme deficiency. A large percentage of fluorouracil is catabolized by the DPD enzyme. DPD enzyme deficiency can result in shunting of fluorouracil to the anabolic pathway, leading to cytotoxic activity and potential toxicities.

EFUDEX is contraindicated in women who are or may become pregnant during therapy. If this drug is used during pregnancy, or if the patient becomes pregnant while using this drug, the patient should be apprised of the potential hazard to the fetus.

EFUDEX is also contraindicated in patients with known hypersensitivity to any of its components.

WARNINGS: Application to mucous membranes should be avoided due to the possibility of local inflammation and ulceration. Additionally, cases of miscarriage and a birth defect (ventricular septal defect) have been reported when EFUDEX was applied to mucous membrane areas during pregnancy.

Occlusion of the skin with resultant hydration has been shown to increase percutaneous penetration of several topical preparations. If any occlusive dressing is used in treatment of basal cell carcinoma, there may be an increase in the severity of inflammatory reactions in the adjacent normal skin. A porous gauze dressing may be applied for cosmetic reasons without increase in reaction.

Exposure to ultraviolet rays should be minimized during and immediately following treatment with EFUDEX because the intensity of the reaction may be increased.

Patients should discontinue therapy with EFUDEX if symptoms of DPD enzyme deficiency develop (see CONTRAINDICATIONS).

Rarely, life-threatening toxicities such as stomatitis, diarrhea, neutropenia, and neurotoxicity have been reported with intravenous administration of fluorouracil in patients with DPD enzyme deficiency. One case of life-threatening systemic toxicity has been reported with the topical use of EFUDEX in a patient with DPD enzyme deficiency. Symptoms included severe abdominal pain, bloody diarrhea, vomiting, fever, and chills. Physical examination revealed stomatitis, erythematous skin rash, neutropenia, thrombocytopenia, inflammation of the esophagus, stomach, and small bowel. Although this case was observed with 5% fluorouracil cream, it is unknown whether patients with profound DPD enzyme deficiency would develop systemic toxicity with lower concentrations of topically applied fluorouracil.

PRECAUTIONS:

General:There is a possibility of increased absorption through ulcerated or inflamed skin.

Information for Patients:Patients should be forewarned that the reaction in the treated areas may be unsightly during therapy and, usually, for several weeks following cessation of therapy. Patients should be instructed to avoid exposure to ultraviolet rays during and immediately following treatment with EFUDEX because the intensity of the reaction may be increased. If EFUDEX is applied with the fingers, the hands should be washed immediately afterward. EFUDEX should not be applied on the eyelids or directly into the eyes, nose, or mouth because irritation may occur.

Fluorouracil, including EFUDEX may be fatal if ingested by pets. Avoid allowing pets to contact the EFUDEX container or the skin where EFUDEX has been applied. Store EFUDEX out of reach of pets. Safely discard or clean any cloth or applicator that may retain EFUDEX and avoid leaving any residues of EFUDEX on your hands, clothing, carpeting or furniture.

Laboratory Tests:Solar keratoses which do not respond should be biopsied to confirm the diagnosis. Follow-up biopsies should be performed as indicated in the management of superficial basal cell carcinoma.

Carcinogenesis, Mutagenesis, Impairment of Fertility:Adequate long-term studies in animals to evaluate carcinogenic potential have not been conducted with fluorouracil. Studies with the active ingredient of EFUDEX, 5-fluorouracil, have shown positive effects in in vitro tests for mutagenicity and on impairment of fertility.

5-Fluorouracil was positive in three in vitro cell neoplastic transformation assays. In the C3H/10T½ clone 8 mouse embryo cell system, the resulting morphologically transformed cells formed tumors when inoculated into immunosuppressed syngeneic mice.

While no evidence for mutagenic activity was observed in the Ames test (three studies), fluorouracil has been shown to be mutagenic in the survival count rec-assay with Bacillus subtilisand in the Drosophila wing-hair spot test. Fluorouracil produced petite mutations in Saccharomyces cerevisiaeand was positive in the micronucleus test (bone marrow cells of male mice).

Fluorouracil was clastogenic in vitro (i.e., chromatid gaps, breaks, and exchanges) in Chinese hamster fibroblasts at concentrations of 1.0 and 2.0 mcg/mL and has been shown to increase sister chromatid exchange in vitro in human lymphocytes. In addition, 5-fluorouracil has been reported to produce an increase in numerical and structural chromosome aberrations in peripheral lymphocytes of patients treated with this product.

Doses of 125 to 250 mg/kg, administered intraperitoneally, have been shown to induce chromosomal aberrations and changes in chromosome organization of spermatogonia in rats. Spermatogonial differentiation was also inhibited by fluorouracil, resulting in transient infertility. However, in studies with a strain of mouse which is sensitive to the induction of sperm head abnormalities after exposure to a range of chemical mutagens and carcinogens, fluorouracil was inactive at oral doses of 5 to 80 mg/kg/day. In female rats, fluorouracil administered intraperitoneally at doses of 25 and 50 mg/kg during the preovulatory phase of oogenesis significantly reduced the incidence of fertile matings, delayed the development of preimplantation and postimplantation embryos, increased the incidence of preimplantation lethality and induced chromosomal anomalies in these embryos. Single-dose intravenous and intraperitoneal injections of 5-fluorouracil have been reported to kill differentiated spermatogonia and spermatocytes (at 500 mg/kg) and to produce abnormalities in spermatids (at 50 mg/kg) in mice.

Pregnancy: See CONTRAINDICATIONS.

Nursing Mothers:It is not known whether EFUDEX is excreted in human milk. Because there is some systemic absorption of fluorouracil after topical administration (see CLINICAL PHARMACOLOGY), because many drugs are excreted in human milk, and because of the potential for serious adverse reactions in nursing infants, a decision should be made whether to discontinue nursing or to discontinue use of the drug, taking into account the importance of the drug to the mother.

Pediatric Use:Safety and effectiveness in children have not been established.

ADVERSE REACTIONS:

The most frequent adverse reactions to EFUDEX occur locally and are often related to an extension of the pharmacological activity of the drug. These include burning, crusting, allergic contact dermatitis, pruritus, scarring, rash, soreness, and ulceration. Ulcerations, other local reactions, cases of miscarriage, and a birth defect (ventricular septal defect) have been reported when EFUDEX was applied to mucous membrane areas. Leukocytosis is the most frequent hematological side effect.

Although a causal relationship is remote, other adverse reactions which have been reported infrequently are:

Central Nervous System:Emotional upset, insomnia, irritability.

Gastrointestinal:Medicinal taste, stomatitis.

Hematological:Eosinophilia, thrombocytopenia, toxic granulation.

Integumentary:Alopecia, blistering, bullous pemphigoid, discomfort, ichthyosis, scaling, suppuration, swelling, telangiectasia, tenderness, urticaria, skin rash.

Special Senses:Conjunctival reaction, corneal reaction, lacrimation, nasal irritation.

Miscellaneous:Herpes simplex.

To report SUSPECTED ADVERSE REACTIONS, contact Bausch Health US, LLC at 1-800-321-4576 and/or FDA at 1-800-FDA-1088 or www.fda.gov/medwatch.

OVERDOSAGE:

There have been no reports of overdosage with EFUDEX.

The oral LD50for the 5% topical cream was 234 mg/kg in rats and 39 mg/kg in dogs. These doses represented 11.7 and 1.95 mg/kg of fluorouracil, respectively. Studies with a 5% topical solution yielded an oral LD50of 214 mg/kg in rats and 28.5 mg/kg in dogs, corresponding to 10.7 and 1.43 mg/kg of fluorouracil, respectively. The topical application of the 5% cream to rats yielded an LD50of greater than 500 mg/kg.

DOSAGE AND ADMINISTRATION:

When EFUDEX is applied to a lesion, a response occurs with the following sequence: erythema, usually followed by vesiculation, desquamation, erosion, and re-epithelialization.

EFUDEX should be applied preferably with a nonmetal applicator or suitable glove. If EFUDEX is applied with the fingers, the hands should be washed immediately afterward.

Actinic or Solar Keratosis:Apply cream or solution twice daily in an amount sufficient to cover the lesions. Medication should be continued until the inflammatory response reaches the erosion stage, at which time use of the drug should be terminated. The usual duration of therapy is from 2 to 4 weeks. Complete healing of the lesions may not be evident for 1 to 2 months following cessation of EFUDEX therapy.

Superficial Basal Cell Carcinomas: Only the 5% strength is recommended.Apply cream or solution twice daily in an amount sufficient to cover the lesions. Treatment should be continued for at least 3 to 6 weeks. Therapy may be required for as long as 10 to 12 weeks before the lesions are obliterated. As in any neoplastic condition, the patient should be followed for a reasonable period of time to determine if a cure has been obtained.

HOW SUPPLIED:

EFUDEX Topical Solution is available in 10 mL drop dispensers containing either 2% (NDC 0187-3202-10) or 5% (NDC 0187-3203-10) fluorouracil and 25 mL drop dispensers containing either 2% (NDC 0187-3202-02) or 5% (NDC 0187-3203-02) fluorouracil on a weight/weight basis compounded with disodium edetate, hydroxypropyl cellulose, methylparaben, propylene glycol, propylparaben, and tris (hydroxymethyl) aminomethane.

EFUDEX Cream is available in 40 g tubes containing 5% fluorouracil (NDC 0187-3204-47) in a vanishing cream base consisting of methylparaben, polysorbate 60, propylene glycol, propylparaben, purified water, stearyl alcohol, and white petrolatum.

Store at 25°C (77°F); excursions permitted to 15° to 30°C (59° to 86°F).

Distributed by:
Bausch Health US, LLC

Bridgewater, NJ 08807 USA

Manufactured by:
Kavis Pharma LLC

Sugar Land, TX 77478 USA

EFUDEX is a trademark of Bausch Health Companies Inc. or its affiliates.

© 2024 Bausch Health Companies Inc. or its affiliates

Rev. 03/2024

9734603

PACKAGE/LABEL PRINCIPAL DISPLAY PANEL-40 g Cream Carton

NDC0187-3204-47

Rx only

Efudex®
(fluorouracil)
Topical Cream
5%

Net Wt. 40 g

FOR TOPICAL USE ONLY

NOT FOR OPHTHALMIC,
ORAL, OR INTRAVAGINAL USE

OrthoDermatologics

Package/Label Display Panel-Solution Carton

PRODUCT DELISTED –

IMAGE NOT AVAILABLE